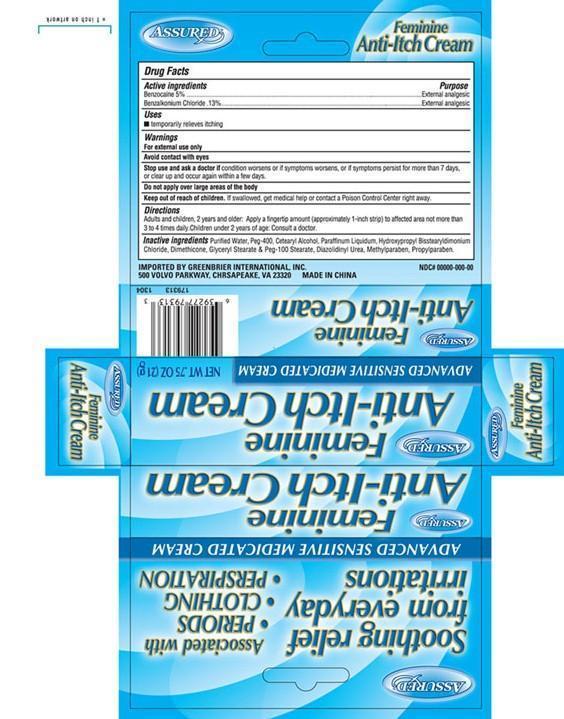 DRUG LABEL: Assured
NDC: 33992-2013 | Form: CREAM
Manufacturer: Greenbrier International
Category: otc | Type: HUMAN OTC DRUG LABEL
Date: 20160808

ACTIVE INGREDIENTS: BENZOCAINE 5 g/100 g; BENZALKONIUM CHLORIDE 130 mg/100 g
INACTIVE INGREDIENTS: WATER; POLYETHYLENE GLYCOL 400; CETOSTEARYL ALCOHOL; MINERAL OIL; HYDROXYPROPYL BISSTEARYLDIMONIUM CHLORIDE; DIMETHICONE; GLYCERYL MONOSTEARATE; PEG-100 STEARATE; DIAZOLIDINYL UREA; METHYLPARABEN; PROPYLPARABEN

Drug Facts

Active Ingredient

Benzocaine 5%

Benzalkonium Chloride .13%

Purpose

External analgesic

Uses

▪ temporarily relieves itching

Warnings

For external use only

Avoid contact with eyes

Stop use and ask a doctor if

condition worsens or if symptoms persist for more than 7 days or clear up and occur again within a few days

Do not apply over large areas of the body

Keep out of reach of children

If swallowed get medical help or contact a Poison Control Center right away

Directions

Adults and children 2 years of age and older: Apply a fingertip amount (approximately 1-inch strip) to affected area not more than 3 to 4 times daily. Children under 2 years of age: Consult a doctor

Inactive Ingredients

Purified water, Peg-400, Cetearyl Alcohol, Paraffinum Liquidum, Hydroxpropyl Bisstearyldimonium Chloride, Dimethicone, Glyceryl Stearate & Peg-100 Stearate, Diaziolidinyl Urea, Methyparaben, Propylparaben